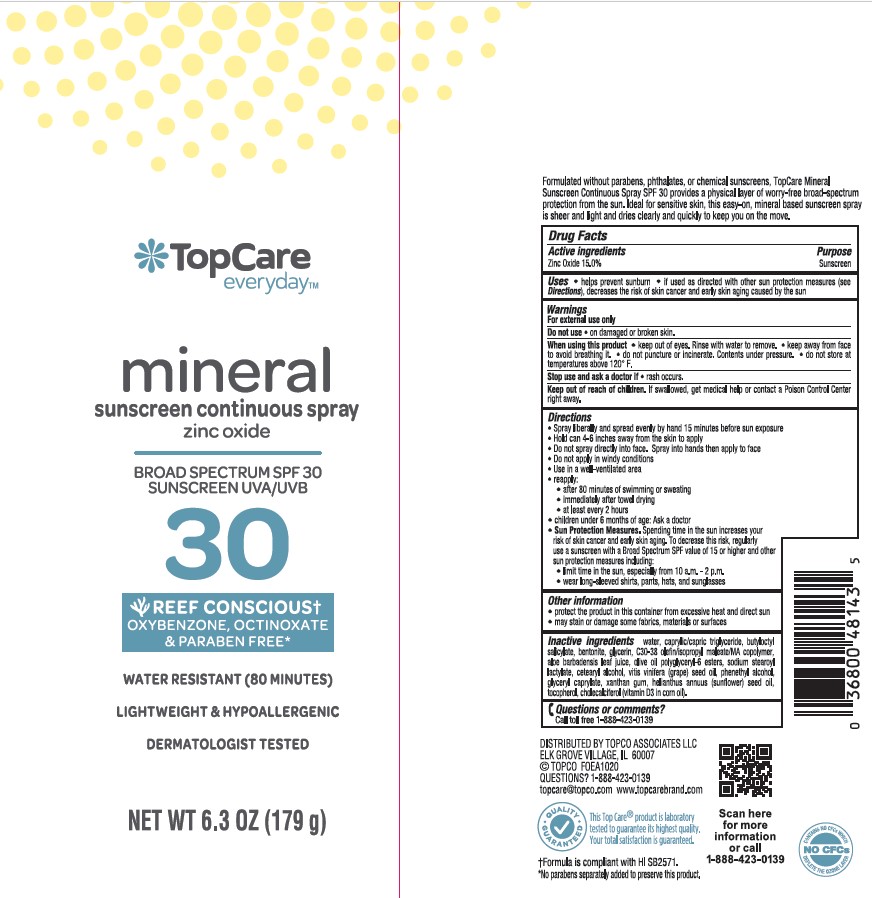 DRUG LABEL: Topco Topcare Everyday Mineral Sunscreen Continuous SPF 30
NDC: 36800-351 | Form: SPRAY
Manufacturer: TOPCO ASSOCIATES LLC
Category: otc | Type: HUMAN OTC DRUG LABEL
Date: 20241015

ACTIVE INGREDIENTS: ZINC OXIDE 150 mg/1 g
INACTIVE INGREDIENTS: WATER; ALOE VERA LEAF; BENTONITE; GLYCERYL CAPRYLATE; .ALPHA.-TOCOPHEROL, DL-; SUNFLOWER OIL; OLIVE OIL POLYGLYCERYL-6 ESTERS; SODIUM STEAROYL LACTYLATE; GLYCERIN; MEDIUM-CHAIN TRIGLYCERIDES; CETOSTEARYL ALCOHOL; BUTYLOCTYL SALICYLATE; CHOLECALCIFEROL; CORN OIL; GRAPE SEED OIL; PHENYLETHYL ALCOHOL; XANTHAN GUM

Topco Topcare Everyday Mineral sunscreen Continuous Spray SPF 30

Active Ingredients

Zinc Oxide 15.0%

Purpose

Sunscreen

Uses

- helps prevent sunburn
- if used as directed with other sun protetion measures (see Directions), decreases the risk of skin cancer and early skin aging caused by the sun

Warnings

For external use only

FLAMMABLE:

- do not use near heat, flame or while smoking
- avoid long term stoage above 104°F (40°C)

Do not use

• on damaged or broken skin.

When using this product

• keep out of eyes. Rinse with water to remove. • do not puncture or incinerate. Contents under pressure. • do not store at temperatures above 120°F.

Stop use and ask a doctor if

• rash occurs.

Keep out of reach of children.

If swallowed, get medical help or contact a Poison Control Center right away.

Directions

- apply liberally 15 minutes before sun exposure
- hold can 4-6 inches away from body, spray evenly to ensure complete coverage
- do not spray into face. Spray into hand and apply to face.
- use in well ventilated, but not windy areas
- reapply:

• after 80 minutes of swimming or sweating

• immediately after towel drying

• at least every 2 hours

- children under 6 months of age: Ask a doctor
- Sun Protection Measures. Spending time in the sun increases your risk of skin cancer and early skin aging. To decrease this risk, regularly use a sunscreen with a Broad Spectrum SPF value of 15 or higher and other sun protection measures including:

• limit time in the sun, especially from 10 a.m. - 2 p.m.

• wearl long-sleeved shirts, pants, hats, and sunglasses

Other Information

- protect the product in this container from excessive heat and direct sun
- may stain or damage some fabrics, materials or surfaces

Inactive Ingredients

Water, Caprylic/Capric Triglyceride, Butyloctyl Salicylate, Bentonite, Glycerin, C30-38 Olefin/Isopropyl Maleate/ MA Copolymer, Aloe Barbadensis Leaf Juice, Olive Oil Polyglyceryl-6 Esters, Sodium Stearoyl Lactylate, Cetearyl Alcohol, Vitis Vinifera (Grape) Seed Oil, Phenethyl Alcohol, Glyceryl Caprylate, Xanthan Gum, Helianthus Annuus (Sunflower) Seed Oil, Zea Mays (Corn) Oil, Tocopherol, Cholecalciferol.